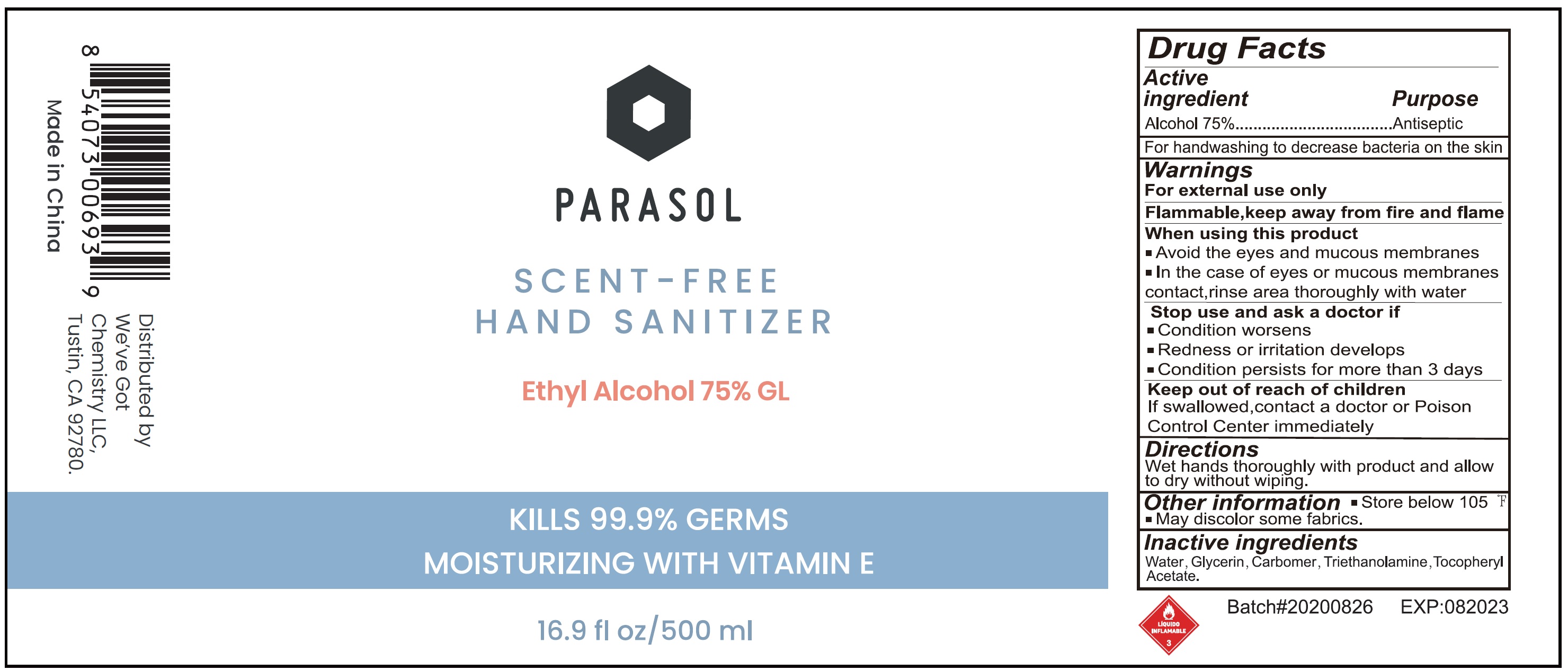 DRUG LABEL: PARASOL SCENT-FREE HAND SANITIZER
NDC: 77446-001 | Form: GEL
Manufacturer: We've Got Chemistry LLC
Category: otc | Type: HUMAN OTC DRUG LABEL
Date: 20231026

ACTIVE INGREDIENTS: ALCOHOL 0.75 mL/1 mL
INACTIVE INGREDIENTS: WATER; GLYCERIN; CARBOMER HOMOPOLYMER, UNSPECIFIED TYPE; TROLAMINE; .ALPHA.-TOCOPHEROL ACETATE

PARASOL SCENT-FREE HAND SANITIZER

Active ingredient

Alcohol 75%

Purpose

Antiseptic

Use

For hand washing to decrease bacteria on the skin

Warnings

For external use only Flammable,keep away from fire and flame

When using this product

- Avoid the eyes and mucous membranes
- In the case of eyes or mucous membranes contact, rinse area thoroughly with water

Stop use and ask a doctor if

- Condition worsens
- Redness or irritation develops
- Condition persista for more than 3 days

Keep out of reach of children

If swallowed, contact a doctor or Poison Control Center immediately

Directions

Wet hands thoroughly with product and allow to dry with out wiping.

Other information

- Store below 105 °F
- May discolor some fabrics.

Inactive ingredients

Water, Glycerin, Carbomer, Triethanolamine, Tocopheryl Acetate.